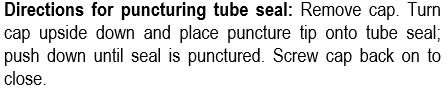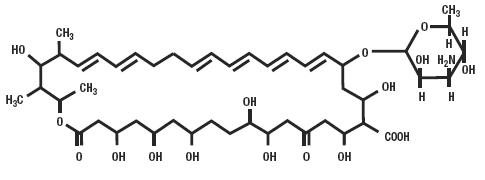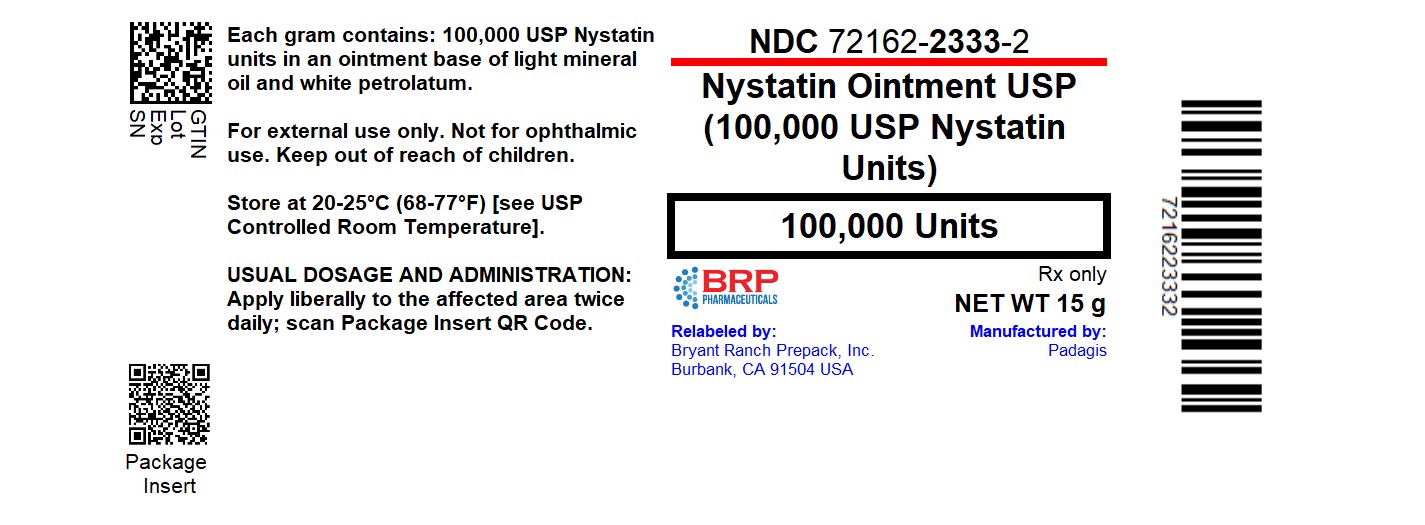 DRUG LABEL: Nystatin
NDC: 72162-2333 | Form: OINTMENT
Manufacturer: Bryant Ranch Prepack
Category: prescription | Type: HUMAN PRESCRIPTION DRUG LABEL
Date: 20250403

ACTIVE INGREDIENTS: NYSTATIN 100000 [USP'U]/1 g
INACTIVE INGREDIENTS: LIGHT MINERAL OIL; PETROLATUM

Nystatin Ointment USP

For Dermatologic Use Only

Not for Ophthalmic Use

Rx Only

DESCRIPTION

Nystatin Ointment USP for topical use only, contains 100,000 USP Nystatin units per gram, in an ointment base of light mineral oil and white petrolatum. The structural formula is as follows:

Molecular Weight 926.13

Molecular Formula C47H75NO17

CLINICAL PHARMACOLOGY

Nystatin is an antifungal antibiotic which is both fungistatic and fungicidal in vitro against a wide variety of yeasts and yeast-like fungi. It probably acts by binding to sterols in the cell membrane of the fungus with a resultant change in membrane permeability allowing leakage of intracellular components. Nystatin is a polyene antibiotic that is obtained from Streptomyces noursei, and is the first well tolerated antifungal antibiotic of dependable efficacy for the treatment of cutaneous, oral and intestinal infections caused by Candida [Monilia]albicans and other Candida species. It exhibits no appreciable activity against bacteria.

Nystatin Ointment USP provides specific therapy for all localized forms of candidiasis. Symptomatic relief is rapid, often occurring within 24 to 72 hours after the initiation of treatment. Cure is effected both clinically and mycologically in most cases of localized candidiasis.

INDICATIONS AND USAGE

Nystatin Ointment USP is indicated in the treatment of cutaneous or mucocutaneous mycotic infections caused by Candida [Monilia]albicans and other Candida species.

CONTRAINDICATIONS

Nystatin Ointment USP is contraindicated in patients with a history of hypersensitivity to any of its components.

PRECAUTIONS

Should a reaction of hypersensitivity occur, the drug should be immediately withdrawn and appropriate measures taken.

This preparation is not for ophthalmic use.

ADVERSE REACTIONS

Nystatin Ointment USP is virtually non-toxic and nonsensitizing and is well tolerated by all age groups including debilitated infants, even on prolonged administration. If irritation on topical application should occur, discontinue medication.

DOSAGE AND ADMINISTRATION

Nystatin Ointment USP should be applied liberally to affected areas twice a day or as indicated until healing is complete. Nystatin cream is usually preferred to nystatin ointment in candidiasis involving intertriginous areas; very moist lesions, however, are best treated with nystatin topical powder.

This preparation does not stain skin or mucous membranes and provides a simple, convenient means of treatment.

HOW SUPPLIED

Nystatin Ointment USP (100,000 USP Nystatin Units per gram) is a yellow ointment available as follows:

- NDC 72162-2333-2: 15 g in a TUBE
- NDC 72162-2333-3: 30 g in a TUBE

STORAGE
Store at 20-25°C (68-77°F) [see USP Controlled Room Temperature].

Repackaged/Relabeled by:
Bryant Ranch Prepack, Inc.
Burbank, CA 91504

PACKAGE LABEL

Nystatin Ointment USP (100,000 USP Nystatin Units)

Extended Label